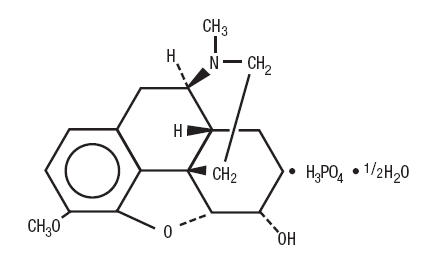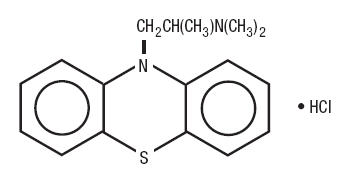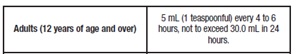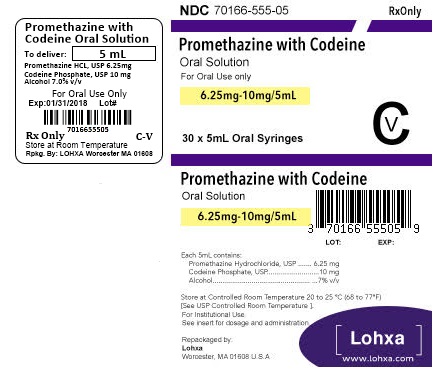 DRUG LABEL: Promethazine with Codeine
NDC: 70166-555 | Form: SOLUTION
Manufacturer: Lohxa
Category: prescription | Type: HUMAN PRESCRIPTION DRUG LABEL
Date: 20180222
DEA Schedule: CV

ACTIVE INGREDIENTS: PROMETHAZINE HYDROCHLORIDE 6.25 mg/5 mL; CODEINE PHOSPHATE 10 mg/5 mL
INACTIVE INGREDIENTS: WATER; TRISODIUM CITRATE DIHYDRATE; EDETATE DISODIUM; SODIUM BENZOATE; SACCHARIN SODIUM; SODIUM PROPIONATE ANHYDROUS; ASCORBIC ACID; ANHYDROUS CITRIC ACID; SODIUM CITRATE; GLYCERIN; ALCOHOL; METHYLPARABEN; FD&C BLUE NO. 1; D&C RED NO. 33; SUCROSE

PROMETHAZINE WITH CODEINE ORAL SOLUTION
CV
(Promethazine Hydrochloride 6.25 mg/5 mL &
Codeine Phosphate 10 mg/5mL)
Rx only

BOXED WARNING

WARNING: ULTRA-RAPID METABOLISM OF CODEINE AND OTHER RISK FACTORS FOR LIFE-THREATENING RESPIRATORY DEPRESSION IN CHILDREN and RISKS FROM CONCOMITANT USE WITH BENZODIAZEPINES OR OTHER CNS DEPRESSANTS

Ultra-Rapid Metabolism of Codeine and Other Risk Factors for Life-Threatening Respiratory Depression in Children

Life-threatening respiratory depression and death have occurred in children who received codeine. Most of the reported cases occurred following tonsillectomy and/or adenoidectomy, and many of the children had evidence of being an ultra-rapid metabolizer of codeine due to a CYP2D6 polymorphism. Promethazine HCl and Codeine Phosphate Oral Solution is contraindicated in children younger than 12 years of age and in children younger than 18 years of age following tonsillectomy and/or adenoidectomy (see CONTRAINDICATIONS). Avoid the use of Promethazine HCl and Codeine Phosphate Oral Solution in adolescents 12 to 18 years of age who have other risk factors that may increase their sensitivity to the respiratory depressant effects of codeine. (See WARNINGS - Ultra-Rapid Metabolism of Codeine and Respiratory Depression).

Promethazine and Respiratory Depression in Children

Postmarketing cases of respiratory depression, including fatalities have been reported with use of promethazine in pediatric patients. Children may be particularly sensitive to the additive respiratory depressant effects when promethazine is combined with other respiratory depressants, including codeine. (See WARNINGS – Promethazine and Respiratory Depression in Children).

Risks from Concomitant Use with Benzodiazepines or Other CNS Depressants

Concomitant use of opioids with benzodiazepines or other central nervous system (CNS) depressants, including alcohol, may result in profound sedation, respiratory depression, coma, and death (see WARNINGS, PRECAUTIONS - Drug Interactions). Avoid use of opioid cough medications in patients taking benzodiazepines, other CNS depressants, or alcohol.

DESCRIPTION

Each 5 mL (one teaspoonful), for oral administration contains: Promethazine hydrochloride 6.25 mg; codeine phosphate 10 mg in a flavored oral solution base with a pH between 4.7 and 5.2. Alcohol 7%.

Inactive Ingredients: Artificial raspberry flavor, ascorbic acid, citric acid anhydrous, D&C Red #33, dehydrated alcohol, edetate disodium, FD&C Blue #1, glycerin, liquid sugar, methylparaben, purified water, saccharin sodium, sodium benzoate, sodium citrate dihydrate and sodium propionate.

Codeine is one of the naturally occurring phenanthrene alkaloids of opium derived from the opium poppy; it is classified pharmacologically as a narcotic analgesic. Codeine phosphate may be chemically designated as 7,8-Didehydro-4,5α-epoxy-3-methoxy-17-methylmorphinan-6α-ol phosphate (1:1)(salt) hemihydrate.

The phosphate salt of codeine occurs as white, needle-shaped crystals or white crystalline powder. Codeine phosphate is freely soluble in water and slightly soluble in alcohol. It has a molecular weight of 406.37, a molecular formula of C18H21NO3•H3PO4•½H2O, and the following structural formula:

Promethazine hydrochloride, a phenothiazine derivative, is chemically designated as (±)-10-[2-(Dimethylamino)propyl] phenothiazine monohydrochloride.

Promethazine hydrochloride occurs as a white to faint yellow, practically odorless, crystalline powder which slowly oxidizes and turns blue on prolonged exposure to air. It is soluble in water and freely soluble in alcohol. It has a molecular weight of 320.88, a molecular formula of C17H20N2S•HCl, and the following structural formula:

CLINICAL PHARMACOLOGY

Codeine

Narcotic analgesics, including codeine, exert their primary effects on the central nervous system and gastrointestinal tract. The analgesic effects of codeine are due to its central action; however, the precise sites of action have not been determined, and the mechanisms involved appear to be quite complex. Codeine resembles morphine both structurally and pharmacologically, but its actions at the doses of codeine used therapeutically are milder, with less sedation, respiratory depression, and gastrointestinal, urinary, and pupillary effects. Codeine produces an increase in biliary tract pressure, but less than morphine or meperidine. Codeine is less constipating than morphine.

Codeine has good antitussive activity, although less than that of morphine at equal doses. It is used in preference to morphine, because side effects are infrequent at the usual antitussive dose of codeine.

Codeine in oral therapeutic dosage does not usually exert major effects on the cardiovascular system.

Narcotic analgesics may cause nausea and vomiting by stimulating the chemoreceptor trigger zone (CTZ); however, they also depress the vomiting center, so that subsequent doses are unlikely to produce vomiting. Nausea is minimal after usual oral doses of codeine.

Narcotic analgesics cause histamine release, which appears to be responsible for wheals or urticaria sometimes seen at the site of injection on parenteral administration. Histamine release may also produce dilation of cutaneous blood vessels, with resultant flushing of the face and neck, pruritus, and sweating.

Codeine and its salts are well absorbed following both oral and parenteral administration. Codeine is about 2/3 as effective orally as parenterally. Codeine is metabolized primarily in the liver by enzymes of the endoplasmic reticulum, where it undergoes O-demethylation, N-demethylation, and partial conjugation with glucuronic acid. The drug is excreted primarily in the urine, largely as inactive metabolites and small amounts of free and conjugated morphine. Negligible amounts of codeine and its metabolites are found in the feces.

Following oral or subcutaneous administration of codeine, the onset of analgesia occurs within 15 to 30 minutes and lasts for four to six hours.

The cough-depressing action, in animal studies, was observed to occur 15 minutes after oral administration of codeine, peak action at 45 to 60 minutes after ingestion. The duration of action, which is dose-dependent, usually did not exceed 3 hours.

Promethazine

Promethazine is a phenothiazine derivative which differs structurally from the antipsychotic phenothiazines by the presence of a branched side chain and no ring substitution. It is thought that this configuration is responsible for its lack (1/10 that of chlorpromazine) of dopamine antagonist properties.

Promethazine is an H1 receptor blocking agent. In addition to its antihistaminic action, it provides clinically useful sedative and antiemetic effects.

Promethazine is well absorbed from the gastrointestinal tract. Clinical effects are apparent within 20 minutes after oral administration and generally last four to six hours, although they may persist as long as 12 hours. Promethazine is metabolized by the liver to a variety of compounds; the sulfoxides of promethazine and N-demethylpromethazine are the predominant metabolites appearing in the urine.

INDICATIONS AND USAGE

Promethazine HCl and Codeine Phosphate Oral Solution is indicated for the temporary relief of coughs and upper respiratory symptoms associated with allergy or the common cold.

CONTRAINDICATIONS

Promethazine HCl and Codeine Phosphate Oral Solution is contraindicated in all children younger than 12 years of age. (See WARNINGS - Ultra- Rapid Metabolism of Codeine and Respiratory Depression).

Promethazine HCl and Codeine Phosphate Oral Solution is contraindicated for postoperative management in children younger than 18 years who have undergone tonsillectomy and/or adenoidectomy. (See WARNINGS - Ultra- Rapid Metabolism of Codeine and Respiratory Depression).

Codeine is contraindicated in patients with a known hypersensitivity to the drug.

Promethazine is contraindicated in comatose states, and in individuals known to be hypersensitive or to have had an idiosyncratic reaction to promethazine or to other phenothiazines.

Antihistamines and codeine are both contraindicated for use in the treatment of lower respiratory tract symptoms, including asthma

WARNINGS

(see Boxed Warnings)

Ultra-Rapid Metabolism of Codeine and Other Risk Factors for Life-threatening Respiratory Depression in Children

Life-threatening respiratory depression and death have occurred in children who received codeine. Codeine is subject to variability in metabolism based upon CYP2D6 genotype (described below), which can lead to an increased exposure to the active metabolite morphine. Based upon post-marketing reports, children younger than 12 years old appear to be more susceptible to the respiratory depressant effects of codeine, particularly if there are risk factors for respiratory depression. For example, many reported cases of death occurred in the post-operative period following tonsillectomy and/or adenoidectomy, and many of the children had evidence of being ultra-rapid metabolizers of codeine. Furthermore, children with obstructive sleep apnea who are treated with codeine for post-tonsillectomy and/or adenoidectomy pain may be particularly sensitive to its respiratory depressant effect.

Because of the risk of life-threatening respiratory depression and death:

- Promethazine HCl and Codeine Phosphate Oral Solution is contraindicated in all children younger than 12 years of age. (See CONTRAINDICATIONS).
- Promethazine HCl and Codeine Phosphate Oral Solution is contraindicated for post-operative management in pediatric patients younger than 18 years of age following tonsillectomy and/or adenoidectomy. (See CONTRAINDICATIONS).
- Avoid the use of Promethazine HCl and Codeine Phosphate Oral Solution in adolescents 12 to 18 years of age who have other risk factors that may increase their sensitivity to the respiratory depressant effects of codeine. Risk factors include conditions associated with hypoventilation, such as postoperative status, obstructive sleep apnea, obesity, severe pulmonary disease, neuromuscular disease, and concomitant use of other medications that cause respiratory depression.
- When prescribing codeine for adolescents, healthcare providers should choose the lowest effective dose for the shortest period of time and inform patients and caregivers about these risks and the signs of morphine overdose. (See OVERDOSAGE).

Nursing Mothers

At least one death was reported in a nursing infant who was exposed to high levels of morphine in breast milk because the mother was an ultra-rapid metabolizer of codeine. Breastfeeding is not recommended during treatment with Promethazine HCl and Codeine Phosphate Oral Solution. (See PRECAUTIONS – Nursing Mothers).

CYP2D6 Genetic Variability: Ultra-rapid metabolizer

Some individuals may be ultra-rapid metabolizers because of a specific CYP2D6 genotype (gene duplications denoted as *1/*1xN or *1/*2xN). The prevalence of this CYP2D6 phenotype varies widely and has been estimated at 1 to 10% for Whites (European, North American), 3 to 4% for Blacks (African Americans), 1 to 2% for East Asians (Chinese, Japanese, Korean), and may be greater than 10% in certain racial/ethnic groups (i.e., Oceanian, Northern African, Middle Eastern, Ashkenazi Jews, Puerto Rican). These individuals convert codeine into its active metabolite, morphine, more rapidly and completely than other people. This rapid conversion results in higher than expected serum morphine levels. Even at labeled dosage regimens, individuals who are ultra-rapid metabolizers may have life-threatening or fatal respiratory depression or experience signs of overdose (such as extreme sleepiness, confusion, or shallow breathing). (See OVERDOSAGE). Therefore, individuals who are ultra-rapid metabolizers should not use Promethazine HCl and Codeine Phosphate Oral Solution.

Promethazine and Respiratory Depression in Children

- Children

Postmarketing cases of respiratory depression, including fatalities have been reported with use of promethazine in pediatric patients. Concomitant administration with other respiratory depressants may increase the risk of respiratory depression. Children may be particularly sensitive to the additive respiratory depressant effects when promethazine is combined with other respiratory depressants, including codeine. See WARNINGS - Ultra-Rapid Metabolism of Codeine and Respiratory Depression for limitations on the use of Promethazine HCl and Codeine Phosphate Oral Solution in children.

Excessively large dosages of antihistamines, including promethazine hydrochloride, in pediatric patients may cause sudden death (see OVERDOSAGE).

• Concomitant Conditions and Other Risk Factors

Avoid use of promethazine in patients at risk for respiratory depression. Risk factors include conditions associated with hypoventilation, such as postoperative status, obstructive sleep apnea, obesity, severe pulmonary disease, neuromuscular disease, and concomitant use of other medications that cause respiratory depression. (See WARNINGS -Risks from Concomitant Use with Benzodiazepines or Other CNS Depressants).

- Risks from Concomitant Use with Benzodiazepines or Other CNS Depressants

Concomitant use of opioids, including Promethazine HCl and Codeine Phosphate Oral Solution, with benzodiazepines, or other CNS depressants, including alcohol, may result in profound sedation, respiratory depression, coma, and death. Because of these risks, avoid use of opioid cough medications in patients taking benzodiazepines, other CNS depressants, or alcohol (see Precautions - Drug Interactions).

Observational studies have demonstrated that concomitant use of opioid analgesics and benzodiazepines increases the risk of drug-related mortality compared to use of opioids alone. Because of similar pharmacologic properties, it is reasonable to expect similar risk with concomitant use of opioid cough medications and benzodiazepines, other CNS depressants, or alcohol.

Advise both patients and caregivers about the risks of respiratory depression and sedation if Promethazine HCl and Codeine Phosphate Oral Solution is used with benzodiazepines, alcohol, or other CNS depressants (see Precautions – Information for Patients).

CNS Depression and Other CNS Effects

- CNS Depression

Promethazine may impair the mental and/or physical abilities required for the performance of potentially hazardous tasks, such as driving a vehicle or operating machinery. The impairment may be amplified by concomitant use of other central-nervous-system depressants such as alcohol, sedatives/hypnotics (including barbiturates), narcotics, narcotic analgesics, general anesthetics, tricyclic antidepressants, and tranquilizers; therefore avoid use of Promethazine HCl and Codeine Phosphate Oral Solution in patients on these medications. (See PRECAUTIONS – Information for Patients and Drug Interactions).

- Convulsions

Convulsions have occurred with therapeutic doses and overdoses of promethazine hydrochloride in pediatric patients. Promethazine may lower seizure threshold. It should be used with caution in persons with seizure disorders or in persons who are using concomitant medications, such as narcotics or local anesthetics, which may also affect seizure threshold.

- Dystonias

Promethazine is a phenothiazine. Phenothiazines are associated with dystonic reactions. In pediatric patients who are acutely ill associated with dehydration, there is an increased susceptibility to dystonias with the use of promethazine HCl.

- Head Injury And Increased Intracranial Pressure

The respiratory depressant effects of narcotic analgesics and their capacity to elevate cerebrospinal fluid pressure may be markedly exaggerated in the presence of head injury, intracranial lesions, or a preexisting increase in intracranial pressure. Narcotics may produce adverse reactions which may obscure the clinical course of patients with head injuries.

Neuroleptic Malignant Syndrome

A potentially fatal symptom complex sometimes referred to as Neuroleptic Malignant

Syndrome (NMS) has been reported in association with promethazine HCl alone or in combination with antipsychotic drugs. Clinical manifestations of NMS are hyperpyrexia, muscle rigidity, altered mental status and evidence of autonomic instability (irregular pulse or blood pressure, tachycardia, diaphoresis and cardiac dysrhythmias).

The diagnostic evaluation of patients with this syndrome is complicated. In arriving at a diagnosis, it is important to identify cases where the clinical presentation includes both serious medical illness (e.g. pneumonia, systemic infection, etc.) and untreated or inadequately treated extrapyramidal signs and symptoms (EPS). Other important considerations in the differential diagnosis include central anticholinergic toxicity, heat stroke, drug fever and primary central nervous system (CNS) pathology.

The management of NMS should include 1) immediate discontinuation of promethazine HCl, antipsychotic drugs, if any, and other drugs not essential to concurrent therapy, 2) intensive symptomatic treatment and medical monitoring, and 3) treatment of any concomitant serious medical problems for which specific treatments are available. There is no general agreement about specific pharmacological treatment regimens for uncomplicated NMS.

Since recurrences of NMS have been reported with phenothiazines, the reintroduction of promethazine HCl should be carefully considered.

Double click here to open Word Application.

Write ordered list in to word document.

Close Word Application.

Pulmonary Consideration

- Asthma and Other Pulmonary Disease

Narcotic analgesics or cough suppressants, including codeine, should not be used in patients with severe asthma or those with frequent asthma attacks (see CONTRAINDICATIONS).

Nor should they be used in acute febrile illness associated with productive cough or in chronic respiratory disease where interference with ability to clear the tracheobronchial tree of secretions would have a deleterious effect on the patient's respiratory function.

- Unresponsive Cough

Dosage of codeine should not be increased if cough fails to respond; an unresponsive cough should be reevaluated in 5 days or sooner for possible underlying pathology, such as foreign body or lower respiratory tract disease.

Cardiovascular Effects

- Hypotension

Codeine may produce orthostatic hypotension in ambulatory patients.

Bone-Marrow Depression

Promethazine should be used with caution in patients with bone-marrow depression. Leukopenia and agranulocytosis have been reported, usually when promethazine HCl has been used in association with other known marrow-toxic agents.

Constipation

Codeine may cause or aggravate constipation.

Other Considerations

Administration of promethazine has been associated with reported cholestatic jaundice.

Administration of codeine may be accomplished by histamine release and should be used with caution in atopic children.

PRECAUTIONS

General

Narcotic analgesics, including codeine, should be administered with caution and the initial dose reduced in patients with acute abdominal conditions, convulsive disorders, significant hepatic or renal impairment, fever, hypothyroidism, Addison's disease, ulcerative colitis, prostatic hypertrophy, in patients with recent gastrointestinal or urinary tract surgery, and in the very young or elderly or debilitated patients.

Promethazine should be used cautiously in persons with cardiovascular disease or with impairment of liver function.

Anticholinergic Effects

Drugs having anticholinergic properties should be used with caution in patients with narrow-angle glaucoma, prostatic hypertrophy, stenosing peptic ulcer, pyloroduodenal obstruction, and bladder-neck obstruction.

Information for Patients

Advise patients of the risks of respiratory depression and death with Promethazine HCl and Codeine Phosphate Oral Solution in children younger than 18 years of age. Advise patients that Promethazine HCl and Codeine Phosphate Oral Solution should not be used in children younger than 12 years of age or in a child younger than 18 years of age for treatment after tonsillectomy and/or adenoidectomy. Advise caregivers of children ages 12 to 18 receiving Promethazine HCl and Codeine Phosphate Oral Solution to monitor for signs of respiratory depression. (See WARNINGS - Ultra-Rapid Metabolism of Codeine and Respiratory Depression).

Advise women that breastfeeding is not recommended during treatment with Promethazine HCl and Codeine Phosphate Oral Solution. (See WARNINGS - Ultra-Rapid Metabolism of Codeine and Respiratory Depression).

Promethazine and codeine may cause marked drowsiness or may impair the mental and/or physical abilities required for the performance of potentially hazardous tasks, such as driving a vehicle or operating machinery. Ambulatory patients should be told to avoid engaging in such activities until it is known that they do not become drowsy or dizzy from promethazine and codeine therapy. Pediatric patients should be supervised to avoid potential harm in bike riding or in other hazardous activities.

Inform patients and caregivers that potentially fatal additive effects may occur if Promethazine HCl and Codeine Phosphate Oral Solution is used with benzodiazepines or other CNS depressants, including alcohol. Because of this risk, patients should avoid concomitant use of Promethazine HCl and Codeine Phosphate Oral Solution with benzodiazepines or other CNS depressants, including alcohol (See WARNINGS- Risks from Concomitant Use with Benzodiazepines or Other CNS Depressants).

Patients should be advised to measure Promethazine HCl and Codeine Phosphate Oral Solution with an accurate measuring device. A household teaspoon is not an accurate measuring device and could lead to overdosage, especially when a half a teaspoon is measured. A pharmacist can recommend an appropriate measuring device and can provide instructions for measuring the correct dose.

Patients should be advised to report any involuntary muscle movements.

Avoid prolonged exposure to the sun.

Codeine, like other narcotic analgesics, may produce orthostatic hypotension in some ambulatory patients. Patients should be cautioned accordingly.

Drug Interactions

Codeine

In patients receiving MAO inhibitors, an initial small test dose is advisable to allow observation of any excessive narcotic effects or MAOI interaction.

The use of benzodiazepines, opioids, antihistamines, antipsychotics, anti-anxiety agents, or other CNS depressants (including alcohol) concomitantly with Promethazine HCl and Codeine Phosphate Oral Solution may cause an additive CNS depressant effect, profound sedation, respiratory depression, coma, and death and should be avoided. (See WARNINGS- Risks from Concomitant Use with Benzodiazepines or Other CNS Depressants).

Promethazine

Epinephrine: Because of the potential for promethazine to reverse epinephrine's vasopressor effect, epinephrine should NOT be used to treat hypotension associated with promethazine overdose.

Anticholinergics: Concomitant use of other agents with anticholinergic properties should be undertaken with caution.

Monoamine Oxidase Inhibitors (MAOI): Drug interactions, including an increased incidence of extrapyramidal effects, have been reported when some MAOI and phenothiazines are used concomitantly.

Drug/Laboratory Test Interactions

Because narcotic analgesics may increase biliary tract pressure, with resultant increase in plasma amylase or lipase levels, determination of these enzyme levels may be unreliable for 24 hours after a narcotic analgesic has been given.

The following laboratory tests may be affected in patients who are receiving therapy with promethazine hydrochloride:

Pregnancy Tests: Diagnostic pregnancy tests based on immunological reactions between HCG and anti-HCG may result in false-negative or false-positive interpretations.

Glucose Tolerance Test: An increase in blood glucose has been reported in patients receiving promethazine.

Carcinogenesis, Mutagenesis, Impairment of Fertility

Long-term animal studies have not been performed to assess the carcinogenic potential of codeine or of promethazine, nor are there other animal or human data concerning carcinogenicity, mutagenicity, or impairment of fertility with these agents. Codeine has been reported to show no evidence of carcinogenicity or mutagenicity in a variety of test systems, including the micronucleus and sperm abnormality assays and the Salmonella assay. Promethazine was nonmutagenic in the Salmonella test system of Ames.

Pregnancy

Teratogenic Effects

Pregnancy Category C

Codeine

A study in rats and rabbits reported no teratogenic effect of codeine administered during the period of organogenesis in doses ranging from 5 to 120 mg/kg. In the rat, doses at the 120-mg/kg level, in the toxic range for the adult animal were associated with an increase in embryo resorption at the time of implantation. In another study a single 100-mg/kg dose of codeine administered to pregnant mice reportedly resulted in delayed ossification in the offspring.

There are no studies in humans, and the significance of these findings to humans, if any, is not known.

Promethazine

Teratogenic effects have not been demonstrated in rat-feeding studies at doses of 6.25 and 12.5 mg/kg of promethazine HCl. These doses are from approximately 2.1 to 4.2 times the maximum recommended total daily dose of promethazine for a 50-kg subject depending upon the indication for which the drug is prescribed. Daily doses of 25 mg/kg intraperitoneally have been found to produce fetal mortality in rats.

Specific studies to test the action of the drug on parturition, lactation, and development of the animal neonate were not done, but a general preliminary study in rats indicated no effect on these parameters. Although antihistamines have been found to produce fetal mortality in rodents, the pharmacological effects of histamine in the rodent do not parallel those in man. There are no adequate and well-controlled studies of promethazine in pregnant women.

Animal reproduction studies have not been conducted with the drug combination – promethazine and codeine. It is not known whether this drug combination can cause fetal harm when administered to a pregnant woman or can affect reproduction capacity. Promethazine HCl and Codeine Phosphate Oral Solution should be given to a pregnant woman only if clearly needed.

Promethazine HCl and Codeine Phosphate Oral Solution should be used during pregnancy only if the potential benefit justifies the potential risk to the fetus.

Nonteratogenic Effects

Dependence has been reported in newborns whose mothers took opiates regularly during pregnancy. Withdrawal signs include irritability, excessive crying, tremors, hyperreflexia, fever, vomiting, and diarrhea. Signs usually appear during the first few days of life.

Promethazine administered to a pregnant woman within two weeks of delivery may inhibit platelet aggregation in the newborn.

Labor and Delivery

Narcotic analgesics cross the placental barrier. The closer to the delivery and the larger the dose used, the greater the possibility of respiratory depression in the newborn. Narcotic analgesics should be avoided during labor if delivery of a premature infant is anticipated. If the mother has received narcotic analgesics during labor, newborn infants should be observed closely for signs of respiratory depression. Resuscitation may be required (see OVERDOSAGE). Limited data suggests that use of promethazine hydrochloride during labor and delivery does not have an appreciable effect on the duration of labor or delivery and does not increase the risk of need for intervention in the newborn The effect of promethazine and/or codeine on later growth and development of the newborn is unknown.

See Nonteratogenic Effects.

Nursing Mothers

Codeine and its active metabolite, morphine, are present in human milk. There are published studies and cases that have reported excessive sedation, respiratory depression, and death (one case) in infants exposed to codeine via breast milk. Women who are ultra-rapid metabolizers of codeine achieve higher than expected serum levels of morphine, potentially leading to higher levels of morphine in breast milk that can be dangerous in their breastfed infants. In women with normal codeine metabolism (normal CYP2D6 activity), the amount of codeine secreted into human milk is low and dose-dependent. There is no information on the effects of the codeine on milk production. Because of the potential for serious adverse reactions, including excess sedation, respiratory depression, and death in a breastfed infant, advise patients that breastfeeding is not recommended during treatment with Promethazine HCl and Codeine Phosphate Oral Solution. (See WARNINGS - Ultra-Rapid Metabolism of Codeine and Respiratory Depression).

If infants are exposed to Promethazine HCl and Codeine Phosphate Oral Solution through breast milk, they should be monitored for excess sedation and respiratory depression. Withdrawal symptoms can occur in breastfed infants when maternal administration of an opioid analgesic is stopped, or when breast-feeding is stopped.

It is not known whether promethazine is excreted in human milk.

Pediatric Use

Life-threatening respiratory depression and death have occurred in children who received codeine. (See WARNINGS - Ultra-Rapid Metabolism of Codeine and Respiratory Depression). Postmarketing cases of respiratory depression, including fatalities have been reported with use of promethazine in pediatric patients. (See WARNINGS – Promethazine and Respiratory Depression in Children). Because of the risk of life-threatening respiratory depression and death:

- Promethazine HCl and Codeine Phosphate Oral Solution is contraindicated in all children younger than age 12 years of age. (See CONTRAINDICATIONS).
- Promethazine HCl and Codeine Phosphate Oral Solution is contraindicated for post-operative management in pediatric patients younger than 18 years of age following tonsillectomy and/or adenoidectomy. (See CONTRAINDICATIONS).
- Avoid the use of Promethazine HCl and Codeine Phosphate Oral Solution in adolescents 12 to 18 years of age who have other risk factors that may increase their sensitivity to the respiratory depressant effects of codeine. Risk factors include conditions associated with hypoventilation, such as postoperative status, obstructive sleep apnea, obesity, severe pulmonary disease, neuromuscular disease, and concomitant use of other medications that cause respiratory depression. (See WARNINGS - Ultra-Rapid Metabolism of Codeine and Respiratory Depression).
- When prescribing codeine for adolescents, healthcare providers should choose the lowest effective dose for the shortest period of time and inform patients and caregivers about these risks and the signs of morphine overdose. (See OVERDOSAGE).

Geriatric Use

Clinical studies of Promethazine HCl and Codeine Phosphate Oral Solution did not include sufficient numbers of subjects aged 65 and over to determine whether they respond differently from younger subjects. Other reported clinical experience has not identified differences in responses between the elderly and younger patients. In general, dose selection for an elderly patient should be cautious, usually starting at the low end of the dosing range, reflecting the greater frequency of decreased hepatic, renal or cardiac function, and of concomitant disease or other drug therapy.

Sedating drugs may cause confusion and over-sedation in the elderly; elderly patients generally should be started on low doses of Promethazine Hydrochloride and Codeine Phosphate Oral Solution and observed closely.

ADVERSE REACTIONS

Call your doctor for medical advice about side effects. You may report side effects to FDA at 1-800-FDA-1088 or www.fda.gov/medwatch.

You may also report side effects to Wockhardt USA, LLC at 1-800-445-4290.

For more information about Promethazine with Codeine Oral Solution, go to www.wockhardtusa.com or call Wockhardt USA, LLC at 1-800-346-6854.

Codeine

Central Nervous System: CNS depression, particularly respiratory depression, and to a lesser extent circulatory depression; light-headedness, dizziness, sedation, euphoria, dysphoria, headache, transient hallucination, disorientation, visual disturbances, and convulsions.

Cardiovascular: Tachycardia, bradycardia, palpitation, faintness, syncope, orthostatic hypotension (common to narcotic analgesics).

Gastrointestinal: Nausea, vomiting, constipation, and biliary tract spasm. Patients with chronic ulcerative colitis may experience increased colonic motility; in patients with acute ulcerative colitis, toxic dilation has been reported.

Genitourinary: Oliguria, urinary retention, antidiuretic effect has been reported (common to narcotic analgesics).

Allergic: Infrequent pruritus, giant urticaria, angioneurotic edema, and laryngeal edema.

Other: Flushing of the face, sweating and pruritus (due to opiate-induced histamine release); weakness.

Promethazine

Central Nervous System: Drowsiness is the most prominent CNS effect of this drug. Sedation, somnolence, blurred vision, dizziness, confusion, disorientation and extrapyramidal symptoms such as oculogyric crisis, torticollis, and tongue protrusion; lassitude, tinnitus, incoordination, fatigue, euphoria, nervousness, diplopia, insomnia, tremors, convulsive seizures, excitation, catatonic-like states, hysteria. Hallucinations have also been reported.

Cardiovascular: Increased or decreased blood pressure, tachycardia, bradycardia, faintness.

Dermatologic: Dermatitis, photosensitivity, urticaria.

Hematologic: Leukopenia, thrombocytopenia, thrombocytopenic purpura, agranulocytosis.

Gastrointestinal: Dry mouth, nausea, vomiting, jaundice.

Respiratory: Asthma, nasal stuffiness, respiratory depression (potentially fatal) and apnea (potentially fatal). (See WARNINGS- Promethazine; Respiratory Depression).

Other: Angioneurotic edema. Neuroleptic malignant syndrome (potentially fatal) has also been reported. (See WARNINGS- Promethazine; Neuroleptic Malignant Syndrome).

Paradoxical Reactions: Hyperexcitability and abnormal movements have been reported in patients following a single administration of promethazine HCl. Consideration should be given to the discontinuation of promethazine HCl and to the use of other drugs if these reactions occur. Respiratory depression, nightmares, delirium and agitated behavior have also been reported in some of these patients.

DRUG ABUSE AND DEPENDENCE

Controlled Substance

Promethazine HCl and Codeine Phosphate Oral Solution is a Schedule V Controlled Substance.

Abuse

Codeine is known to be subject to abuse; however, the abuse potential of oral codeine appears to be quite low. Even parenteral codeine does not appear to offer the psychic effects sought by addicts to the same degree as heroin or morphine. However, codeine must be administered only under close supervision to patients with a history of drug abuse or dependence.

Dependence

Psychological dependence, physical dependence, and tolerance are known to occur with codeine.

OVERDOSAGE

Codeine

Serious overdose with codeine is characterized by respiratory depression (a decrease in respiratory rate and/or tidal volume, Cheyne-stokes respiration, cyanosis), extreme somnolence progressing to stupor or coma, skeletal muscle flaccidity, cold and clammy skin, and sometimes bradycardia and hypotension. The triad of coma, pinpoint pupils, and respiratory depression is strongly suggestive of opiate poisoning. In severe overdosage, particularly by the intravenous route, apnea, circulatory collapse, cardiac arrest, and death may occur. Promethazine is additive to the depressant effects of codeine.

It is difficult to determine what constitutes a standard toxic or lethal dose. However, the lethal oral dose of codeine in an adult is reported to be in the range of 0.5 to 1 gram. Infants and children are believed to be relatively more sensitive to opiates on a body-weight basis. Elderly patients are also comparatively intolerant to opiates.

Promethazine

Signs and symptoms of overdosage with promethazine range from mild depression of the central nervous system and cardiovascular system to profound hypotension, respiratory depression, unconsciousness and sudden death. Other reported reactions include hyperreflexia, hypertonia, ataxia, athetosis and extensor-plantar reflexes (Babinski reflex).

Stimulation may be evident, especially in children and geriatric patients. Convulsions may rarely occur. A paradoxical reaction has been reported in children receiving single doses of 75 mg to 125 mg orally, characterized by hyperexcitability and nightmares.

Atropine-like signs and symptoms - dry mouth, fixed dilated pupils, flushing, as well as gastrointestinal symptoms, may occur.

Treatment

Treatment of overdosage with promethazine and codeine is essentially symptomatic and supportive. Only in cases of extreme overdosage or individual sensitivity do vital signs including respiration, pulse, blood pressure, temperature, and EKG need to be monitored. Activated charcoal orally or by lavage may be given, or sodium or magnesium sulfate orally as a cathartic. Attention should be given to the reestablishment of adequate respiratory exchange through provision of a patent airway and institution of assisted or controlled ventilation. The narcotic antagonist, naloxone hydrochloride, may be administered when significant respiratory depression occurs with promethazine and codeine; any depressant effects of promethazine are not reversed with naloxone. Diazepam may be used to control convulsions. Avoid analeptics, which may cause convulsions. Acidosis and electrolyte losses should be corrected. A rise in temperature or pulmonary complications may signal the need for institution of antibiotic therapy.

Severe hypotension usually responds to the administration of norepinephrine or phenylephrine. EPINEPHRINE SHOULD NOT BE USED, since its use in a patient with partial adrenergic blockade may further lower the blood pressure.

Limited experience with dialysis indicates that it is not helpful.

DOSAGE AND ADMINISTRATION

It is important that Promethazine HCl and Codeine Phosphate Oral Solution is measured with an accurate measuring device (see PRECAUTIONS - Information for Patients). A household teaspoon is not an accurate measuring device and could lead to overdosage, especially when half a teaspoon is to be measured. It is strongly recommended that an accurate measuring device be used. A pharmacist can provide an appropriate device and can provide instructions for measuring the correct dose.

Promethazine HCl and Codeine Phosphate is contraindicated in pediatric patients less than 6 years of age, because the combination may cause fatal respiratory depression in this age population.

The average effective dose is given in the following table:

HOW SUPPLIED

Promethazine with Codeine Oral Solution contains promethazine hydrochloride 6.25 mg/5 mL, codeine phosphate 10 mg/5 mL and alcohol 7 percent.

Single Use Pre-Filled Unit Dose Syringe.

Store at 20° – 25°C (68° – 77°F) [see USP Controlled Room Temperature].

Protect from light.

Rx Only

Distributed By:

Lohxa

Worcester, MA 01608

REV. 02-18

MEDICATION GUIDE

Promethazine (proe METH a zeen) with Codeine (KOE deen) Oral Solution, CV

(Promethazine Hydrochloride and Codeine Phosphate Oral Solution)

What is the most important information I should know about Promethazine Hydrochloride and Codeine Phosphate Oral Solution?

- Promethazine Hydrochloride and Codeine Phosphate Oral Solution can cause children to stop breathing (respiratory depression) and cause death.
  - Do not give Promethazine Hydrochloride and Codeine Phosphate Oral Solution to children younger than 12 years of age, or to children younger than 18 years of age after tonsillectomy or adenoidectomy surgery.
  - You should not give Promethazine Hydrochloride and Codeine Phosphate Oral Solution to children between 12 to 18 years of age who have certain risk factors for breathing problems, including:
    - recent surgery
    - obstructive sleep apnea
    - are obese
    - severe lung problems
    - other medical conditions that can cause difficulty breathing, such as neuromuscular problems
    - taking other medicines that cause breathing problems
- You should not breastfeed during treatment with Promethazine Hydrochloride and Codeine Phosphate Oral Solution because it may cause your child to stop breathing and cause death.
- Severe drowsiness, breathing problems (respiratory depression), coma, and death can happen in adults and children who take Promethazine Hydrochloride and Codeine Phosphate Oral Solution with benzodiazepines, or other central nervous system depressants, including alcohol.
  - Avoid taking other medicines that can cause drowsiness or sleepiness, or drinking alcohol during treatment with Promethazine Hydrochloride and Codeine Phosphate Oral Solution. Ask your healthcare provider for a list of these medicines if you are not sure.
- Promethazine Hydrochloride and Codeine Phosphate Oral Solution can cause breathing problems (respiratory depression) and drowsiness.
  - Take Promethazine Hydrochloride and Codeine Phosphate Oral Solution exactly as prescribed by your healthcare provider. If you take the wrong dose of Promethazine Hydrochloride and Codeine Phosphate Oral Solution you could overdose and die. See the Medication Guide section called "How should I take Promethazine Hydrochloride and Codeine Phosphate Oral Solution?" for important information about how to take Promethazine Hydrochloride and Codeine Phosphate Oral Solution correctly.
  - Avoid driving a car or operating machinery during treatment with Promethazine Hydrochloride and Codeine Phosphate Oral Solution.
- Call your healthcare provider or get emergency medical help right away if anyone taking Promethazine Hydrochloride and Codeine Phosphate Oral Solution, or your breastfeeding baby has any of the symptoms below:
  - increased sleepiness
  - confusion
  - difficulty breathing
  - shallow breathing
  - limpness
  - your baby has difficulty breastfeeding
- Keep Promethazine Hydrochloride and Codeine Phosphate Oral Solution in a safe place away from children. Accidental use by a child is a medical emergency and can cause death. If a child accidentally takes Promethazine Hydrochloride and Codeine Phosphate Oral Solution, get emergency medical help right away.

What is Promethazine Hydrochloride and Codeine Phosphate Oral Solution?

- Promethazine Hydrochloride and Codeine Phosphate Oral Solution is a prescription medicine used to temporarily treat cough and upper respiratory symptoms, including a stuffy nose (nasal congestion) that you can have with allergies or a common cold. Promethazine Hydrochloride and Codeine Phosphate Oral Solution contains 2 medicines, promethazine and codeine. Promethazine is an antihistamine. Codeine is a narcotic cough suppressant.
- Promethazine Hydrochloride and Codeine Phosphate Oral Solution is a federal controlled substance (C-V) because it contains codeine that can be abused or lead to dependence. Keep Promethazine Hydrochloride and Codeine Phosphate Oral Solution in a safe place to prevent misuse and abuse. Selling or giving away Promethazine Hydrochloride and Codeine Phosphate Oral Solution may harm others, and is against the law. Tell your healthcare provider if you have ever abused or been dependent on alcohol, prescription medicines or street drugs
- Promethazine Hydrochloride and Codeine Phosphate Oral Solution is not for children under 12 years of age.

Who should not take Promethazine Hydrochloride and Codeine Phosphate Oral Solution?

- Do not give Promethazine Hydrochloride and Codeine Phosphate Oral Solution to children younger than 12 years of age.
- Do not give Promethazine Hydrochloride and Codeine Phosphate Oral Solution to children younger than 18 years of any age after tonsillectomy or adenoidectomy surgery.
- Do not take Promethazine Hydrochloride and Codeine Phosphate Oral Solution if you are allergic to any of the ingredients in Promethazine Hydrochloride and Codeine Phosphate Oral Solution. See the end of this Medication Guide for a complete list of ingredients in Promethazine Hydrochloride and Codeine Phosphate Oral Solution.
- Do not take Promethazine Hydrochloride and Codeine Phosphate Oral Solution if you have asthma.
- Do not take Promethazine Hydrochloride and Codeine Phosphate Oral Solution if you have high blood pressure or narrowing of blood vessels to your legs or arms (peripheral vascular insufficiency).
- Do not take Promethazine Hydrochloride and Codeine Phosphate Oral Solution if you take a medicine called a Monoamine Oxidase Inhibitor (MAOI).

Before you take Promethazine Hydrochloride and Codeine Phosphate Oral Solution, tell your healthcare provider about all of your medical conditions, including if you:

- have a drug dependence
- have lung or breathing problems including chronic obstructive pulmonary disease (COPD), or sleep apnea.
- have had a head injury
- have pain in your stomach-area (abdomen)
- have a history of severe or persistent cough
- have prostate problems
- have problems with your urinary tract (urethral stricture) or difficulty urinating
- have had surgery recently or plan to have surgery
- drink alcohol
- have kidney or liver problems
- have thyroid problems including hypothyroidism
- have Addison's disease
- have glaucoma (increased pressure in eyes)
- have diabetes
- have seizures
- have heart problems or blood vessel (cardiovascular) problems including high blood pressure or peripheral vascular insufficiency See " Who should not take Promethazine Hydrochloride and Codeine Phosphate Oral Solution?
- have blood disorders including low white blood cells
- are pregnant or plan to become pregnant. It is not known if Promethazine Hydrochloride and Codeine Phosphate Oral Solution will harm your unborn baby. You and your healthcare provider should decide if you should take Promethazine Hydrochloride and Codeine Phosphate Oral Solution while you are pregnant.
- are breastfeeding or plan to breastfeed. Codeine Phosphate passes into your breast milk and may harm your baby. It is not known if Promethazine Hydrochloride can pass into your breast milk. You should not breastfeed during treatment with Promethazine Hydrochloride and Codeine Phosphate Oral Solution.

Tell your healthcare provider about all the medicines you take, including prescription and over-the-counter medicines, vitamins, and herbal supplements.

Taking Promethazine Hydrochloride and Codeine Phosphate Oral Solution with certain other medicines can cause side effects or affect how well Promethazine Hydrochloride and Codeine Phosphate Oral Solution or the other medicines work. Do not start or stop other medicines without talking to your healthcare provider. Especially tell your healthcare provider if you:

- take pain medicines such as narcotics
- take cold or allergy medicines that contain antihistamines or cough suppressants
- take medicines for mental illness (anti-psychotics, anti-anxiety)
- drink alcohol
- take medicines for depression, including monoamine oxidase inhibitors (MAOIs) or tricyclic antidepressants (TCAs)
- take medicines for stomach or intestinal problems
- take ergot containing medicines
- take medicines called alpha blockers
- take medicines called beta blockers
- take stimulants or uppers (amphetamines)

Ask your healthcare provider if you are not sure if you take one of these medicines.

How should I take Promethazine Hydrochloride and Codeine Phosphate Oral Solution?

- Take Promethazine Hydrochloride and Codeine Phosphate Oral Solution exactly as your healthcare provider tells you to take it.
- Your healthcare provider will tell you how much Promethazine Hydrochloride and Codeine Phosphate Oral Solution to take and when to take it. Do not change your dose without talking to your healthcare provider.
- Ask your pharmacist to give you a measuring device to help you measure the correct amount of Promethazine Hydrochloride and Codeine Phosphate Oral Solution. Do not use a household teaspoon to measure your medicine. You may accidently take too much.
- Do not take more than 30 mL of Promethazine Hydrochloride and Codeine Phosphate Oral Solution in 24 hours.
- If you take too much Promethazine Hydrochloride and Codeine Phosphate Oral Solution, call your healthcare provider or go to the nearest hospital emergency room right away.

What should I avoid while taking Promethazine Hydrochloride and Codeine Phosphate Oral Solution?

- Promethazine Hydrochloride and Codeine Phosphate Oral Solution can cause you to be drowsy. Avoid driving a car or operating machinery during the treatment with Promethazine Hydrochloride and Codeine Phosphate Oral Solution. Also, watch your child closely when riding a bike.
- Avoid drinking alcohol during the treatment with Promethazine Hydrochloride and Codeine Phosphate Oral Solution. Drinking alcohol can increase your chances of having serious side effects.
- Avoid spending a long time in sunlight.

What are the possible side effects of Promethazine Hydrochloride and Codeine Phosphate Oral Solution? Promethazine Hydrochloride and Codeine Phosphate Oral Solution may cause serious side effects, including:

- See "What is the most important information I should know about Promethazine Hydrochloride and Codeine Phosphate Oral Solution?"
- Breathing problems (respiratory depression) which can lead to death. Call your healthcare provider or get emergency treatment right away if you have excessive sleepiness, shallow or slow breathing, or confusion.
- Physical dependence or abuse. Take Promethazine Hydrochloride and Codeine Phosphate Oral Solution exactly as your healthcare provider tells you to take it. Stopping Promethazine Hydrochloride and Codeine Phosphate Oral Solution suddenly could cause withdrawal symptoms.
- Bowel problems including constipation or stomach pain.
- Increased intracranial pressure.
- Feeling dizzy, faint or light-headed, especially when you stand up (orthostatic hypotension) . Light-headedness or fainting may happen when getting up too quickly from a sitting or lying position.
- Neuroleptic malignant syndrome (NMS) which can lead to death. Tell you healthcare provider right away if you have any of the following symptoms of NMS:
  - high fever
  - stiff muscles
  - confusion
  - sweating
  - changes in pulse, heart rate, and blood pressure

The most common side effects of Promethazine Hydrochlorde and Codeine Phosphate Oral Solution include:

- sleepiness
- confusion
- dryness of mouth, nose, throat
- nausea and vomiting
- difficulty urinating
- trouble breathing
- high blood pressure
- restlessness
- fast heart beat

These are not all the possible side effects of Promethazine Hydrochloride and Codeine Phosphate Oral Solution. Call your doctor for medical advice about side effects. You may report side effects to FDA at 1-800-FDA- 1088.

How should I store Promethazine Hydrochloride and Codeine Phosphate Oral Solution?

- Store Promethazine Hydrochloride and Codeine Phosphate Oral Solution at room temperature between 68°F to 77°F (20°C to 25°C).
- Keep Promethazine Hydrochloride and Codeine Phosphate Oral Solution in a tightly closed, child-resistant container and out of the light.
- Safely throw away medicine that is out of date or no longer needed.
- Keep Promethazine Hydrochloride and Codeine Phosphate Oral Solution and all medicines out of the reach of children.

General information about the safe and effective use of Promethazine Hydrochloride and Codeine Phosphate Oral Solution.

Medicines are sometimes prescribed for purposes other than those listed in a Medication Guide. Do not use Promethazine Hydrochloride and Codeine Phosphate Oral Solution for a condition for which it was not prescribed. Do not give Promethazine Hydrochloride and Codeine Phosphate Oral Solution to other people, even if they have the same symptoms that you have. It may harm them.

You can ask your pharmacist or healthcare provider for information about Promethazine Hydrochloride and Codeine Phosphate Oral Solution that is written for health professionals.

What are the ingredients in Promethazine Hydrochloride and Codeine Phosphate Oral Solution?

Active ingredients: promethazine hydrochloride and codeine phosphate

Inactive ingredients: Artificial raspberry flavor, ascorbic acid, citric acid anhydrous, D&C Red #33, dehydrated alcohol, edetate disodium, FD&C Blue #1, glycerin, liquid sugar, methylparaben, purified water, saccharin sodium, sodium benzoate, sodium citrate dihydrate and sodium propionate.

Manufactured For:

Wockhardt USA, LLC

Parsippany, NJ 07054

Manufactured By:

Morton Grove Pharmaceuticals, Inc.

Morton Grove, IL 60053

26606P

Rev. 11-17

For more information, go to www.wockhardtusa.com or call Wockhardt USA, LLC at 1-800-346-6854.

This Medication Guide has been approved by the U.S. Food and Drug Administration.

PRINCIPAL DISPLAY PANEL

NDC 70166-555-05

PROMETHAZINE WITH CODEINE ORAL SOLUTION

(Promethazine Hydrochloride 6.25 mg/5mL & Codeine Phosphate 10 mg/5 mL) CV

(Contains alcohol 7.0% v/v)

Rx Only